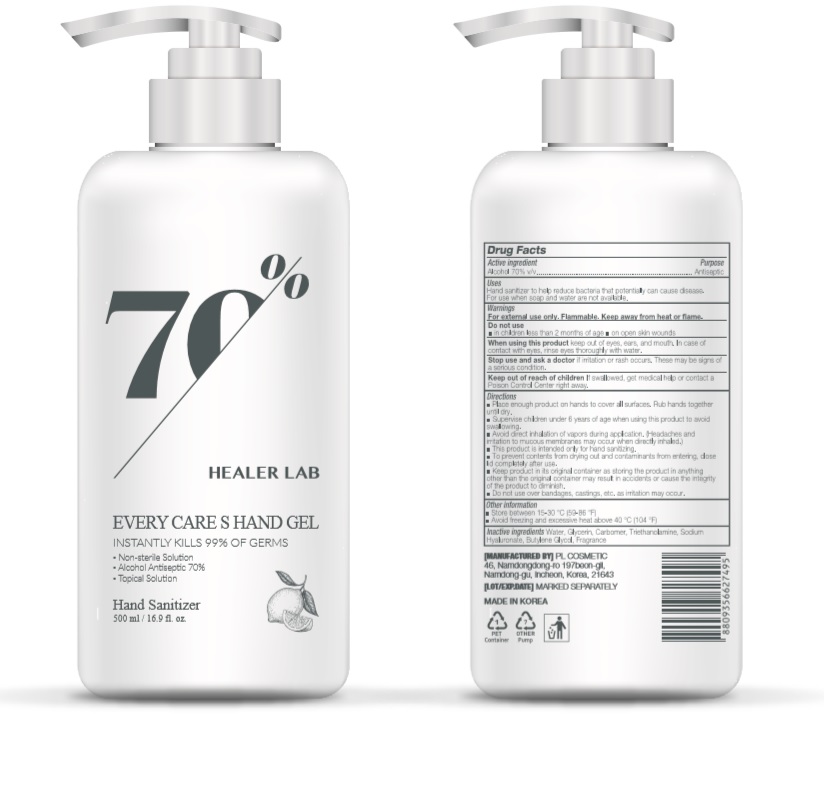 DRUG LABEL: HEALER LAB EVERY CARE S HAND Gel
NDC: 74339-8500 | Form: GEL
Manufacturer: PL COSMETIC
Category: otc | Type: HUMAN OTC DRUG LABEL
Date: 20200407

ACTIVE INGREDIENTS: ALCOHOL 350 mL/500 mL
INACTIVE INGREDIENTS: GLYCERIN; CARBOMER HOMOPOLYMER, UNSPECIFIED TYPE; WATER; BUTYLENE GLYCOL; HYALURONATE SODIUM; TROLAMINE

[HEALER LAB EVERY CARE S HAND GEL] 500 ml : 74339-8500